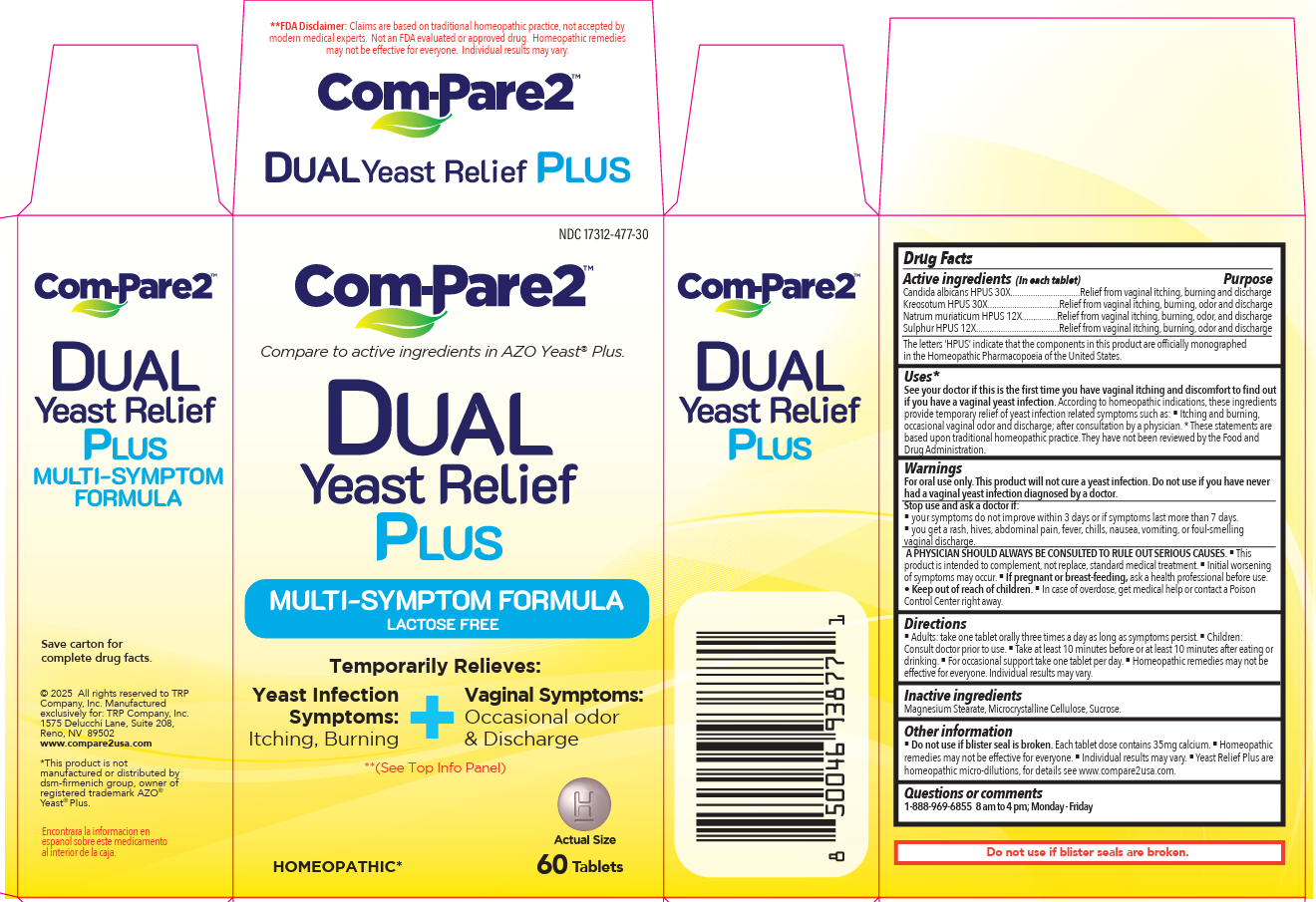 DRUG LABEL: Com-Pare2 Dual Yeast Relief Plus
NDC: 17312-477 | Form: TABLET
Manufacturer: TRP Company
Category: homeopathic | Type: HUMAN OTC DRUG LABEL
Date: 20251103

ACTIVE INGREDIENTS: CANDIDA ALBICANS 30 [hp_X]/1 1; WOOD CREOSOTE 30 [hp_X]/1 1; SODIUM CHLORIDE 12 [hp_X]/1 1; SULFUR 12 [hp_X]/1 1
INACTIVE INGREDIENTS: CELLULOSE, MICROCRYSTALLINE; MAGNESIUM STEARATE; SUCROSE

Com-Pare2 Dual Yeast Relief Plus

Active Ingredients (in each tablet):

Candida albicans 30X

Kreosotum 30X

Natrium muriaticum 12X

Sulphur 12X

Purpose

Candida albicans - Relief from vaginal itching, burning and discharge

Kreosotum - Relief from vaginal itching, burning, odor and discharge

Natrum muriaticum - Relief from vaginal itching, burning, odor, and discharge

Sulphur - Relief from vaginal itching, burning, odor and discharge

Uses*

See your doctor if this is the first time you have vaginal itching and discomfort to find out if you have a vaginal yeast infection. According to homeopathic indications, these ingredients provide temporary relief of yeast infection related symptoms such as:

- Itching and burning, occasional vaginal odor and discharge; after consultation by a physician.

* These statements are based upon traditional homeopathic practice. They have not been reviewed by the Food and Drug Administration.

Warnings:

For oral use only. This product will not cure a yeast infection.

Do not use if you have never had a vaginal yeast infection diagnosed by a doctor.

Stop use and ask a doctor if:

- your symptoms do not improve within 3 days or if symptoms last more than 7 days.
- you get a rash, hives, abdominal pain, fever, chills, nausea, vomiting, or foul-smelling vaginal discharge.

ASK DOCTOR

A PHYSICIAN SHOULD ALWAYS BE CONSULTED TO RULE OUT SERIOUS CAUSES.

- This product is intended to complement, not replace, standard medical treatment.
- Initial worsening of symptoms may occur.

PREGNANCY OR BREAST FEEDING

- If pregnant or breast-feeding, ask a health professional before use.

• Keep out of reach of children. In case of overdose, get medical help or contact a Poison Control Center right away.

Directions:

- Adults: take one tablet orally three times a day as long as symptoms persist.
- Children: consult a physician prior to use.
- Take at least 10 minutes before or at least 10 minutes after eating or drinking.
- For occasional support take one tablet per day.
- Homeopathic remedies may not be effective for everyone. Individual results may vary.

Inactive Ingredients

Magnesium Stearate, Microcrystalline Cellulose, Sucrose.

Other Information:

- Do not use if blister seal is broken. Each tablet dose contains 35mg calcium.
- Homeopathic remedies may not be effective for everyone.
- Individual results may vary.
- Yeast Relief Plus are homeopathic micro-dilutions, for details see www.compare2usa.com.

Questions or comments

1-888-969-6855 8 am to 4 pm; Monday - Friday